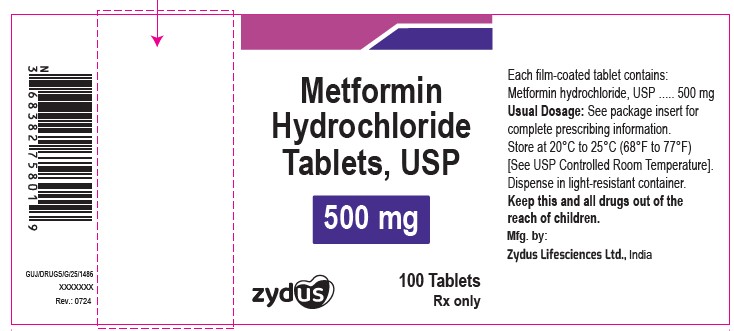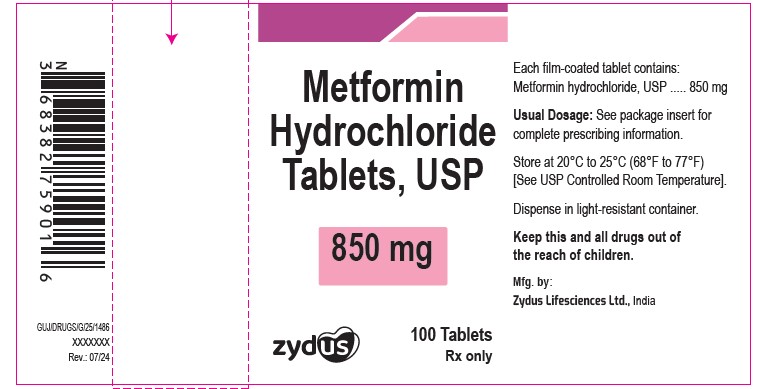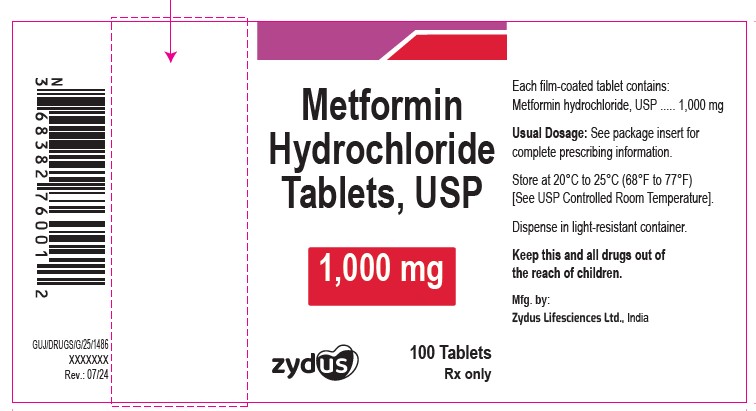 DRUG LABEL: METFORMIN HYDROCHLORIDE
NDC: 65841-809 | Form: TABLET, FILM COATED
Manufacturer: Zydus Lifesciences Limited
Category: prescription | Type: HUMAN PRESCRIPTION DRUG LABEL
Date: 20241205

ACTIVE INGREDIENTS: METFORMIN HYDROCHLORIDE 500 mg/1 1
INACTIVE INGREDIENTS: HYPROMELLOSES; MAGNESIUM STEARATE; POLYETHYLENE GLYCOL, UNSPECIFIED; POVIDONE; CELLULOSE, MICROCRYSTALLINE; SILICON DIOXIDE; SODIUM STARCH GLYCOLATE TYPE A POTATO

METFORMIN HYDROCHLORIDE TABLETS

PACKAGE LABEL.PRINCIPAL DISPLAY PANEL

NDC 65841-809-01 in bottle of 100 tablets

Metformin Hydrochloride Tablets USP, 500 mg

Rx only

100 tablets

NDC 65841-810-01 in bottle of 100 tablets

Metformin Hydrochloride Tablets USP, 850 mg

Rx only

100 tablets

NDC 65841-811-01 in bottle of 100 tablets

Metformin Hydrochloride Tablets USP, 1000 mg

Rx only

100 tablets